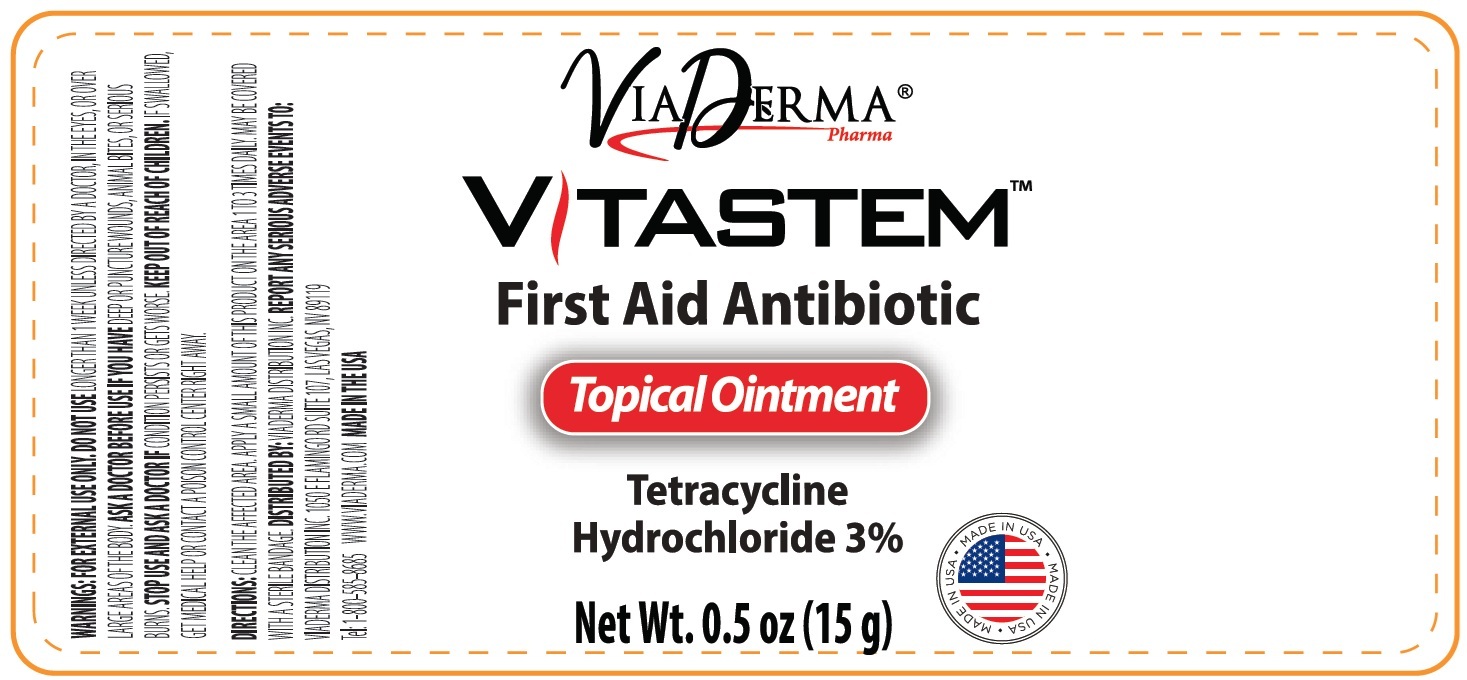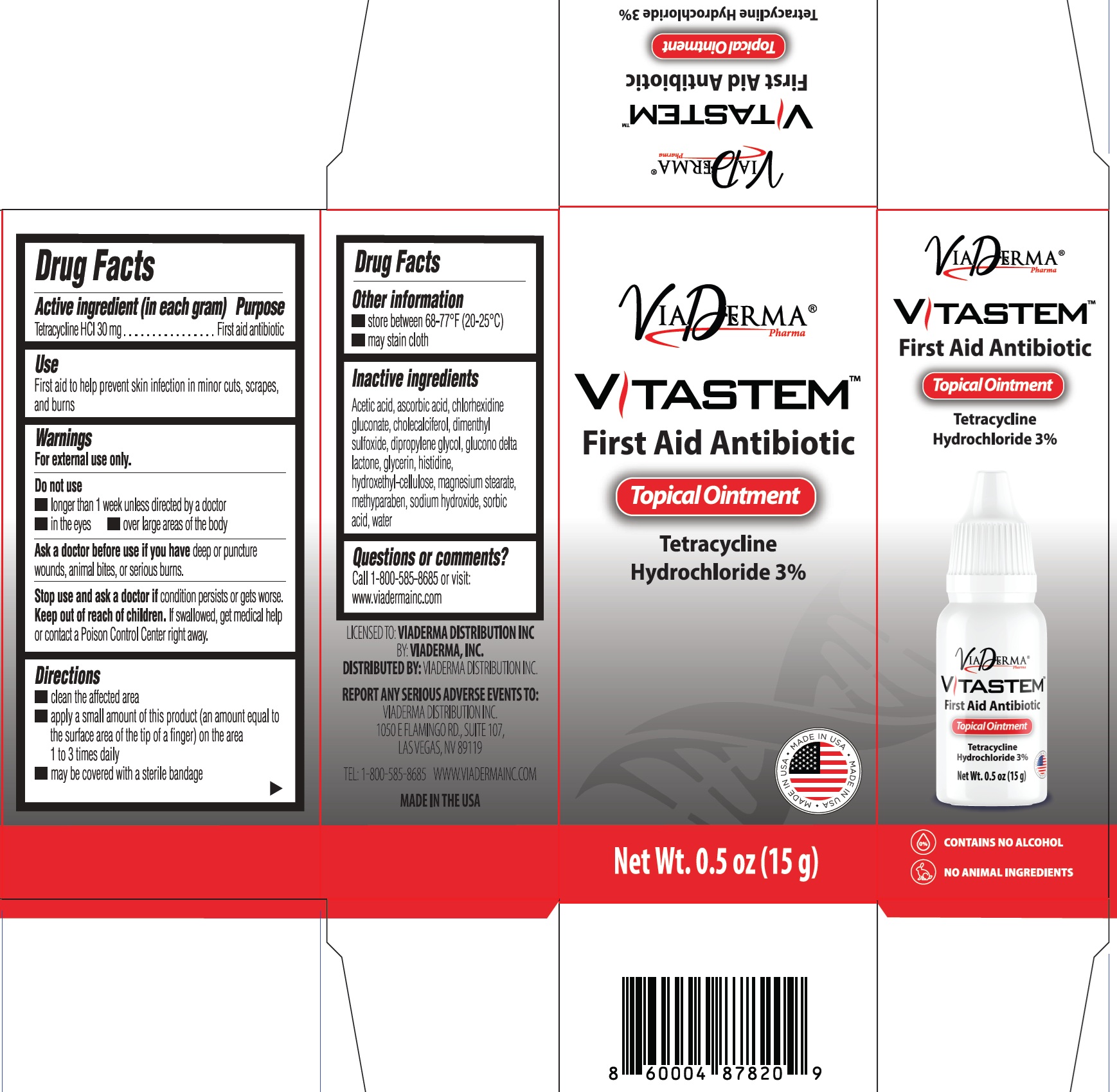 DRUG LABEL: Vitastem First Aid Antibiotic
NDC: 71262-012 | Form: OINTMENT
Manufacturer: VIADERMA DISTRIBUTION INC
Category: otc | Type: HUMAN OTC DRUG LABEL
Date: 20251202

ACTIVE INGREDIENTS: TETRACYCLINE HYDROCHLORIDE 30 mg/1 g
INACTIVE INGREDIENTS: ACETIC ACID; ASCORBIC ACID; CHLORHEXIDINE GLUCONATE; CHOLECALCIFEROL; DIMETHYL SULFOXIDE; DIPROPYLENE GLYCOL; GLUCONOLACTONE; GLYCERIN; HISTIDINE; HYDROXYETHYL CELLULOSE, UNSPECIFIED; MAGNESIUM STEARATE; METHYLPARABEN; SODIUM HYDROXIDE; SORBIC ACID; WATER

Vitastem First Aid Antibiotic

Active ingredient (in each gram)

Tetracyline HCl 30 mg

Purpose

First aid antibiotic

Use

First aid to help prevent skin infection in minor cuts, scrapes, and burns

Warnings

For external use only.

Do not use

• longer than 1 week unless directed by a doctor

• in the eyes

• over large areas of the body

Ask a doctor before use if you have

deep or puncture wounds, animal bites, or serious burns.

Stop use and ask a doctor if

condition persists or gets worse.

Keep out of reach of children.

If swallowed, get medical help or contact a Poison Control Center right away.

Directions

- clean the affected area
- apply a small amount of this product (an amount equal to the surface area of the tip of a finger) on the area 1 to 3 times daily
- may be covered with a sterile bandage

Other information

- store between 68-77°F (20-25°C)
- may stain cloth

Inactive ingredients

Acetic acid, ascorbic acid, chlorhexidine gluconate, cholecalciferol, dimethyl sulfoxide, dipropylene glycol, glucono delta lactone, glycerin, histidine, hydroxethyl cellulose, magnesium stearate, methylparaben, sodium hydroxide, sorbic acid, water

Questions or comments?

Call 1-800-585-8685 or visit: www.viadermainc.com